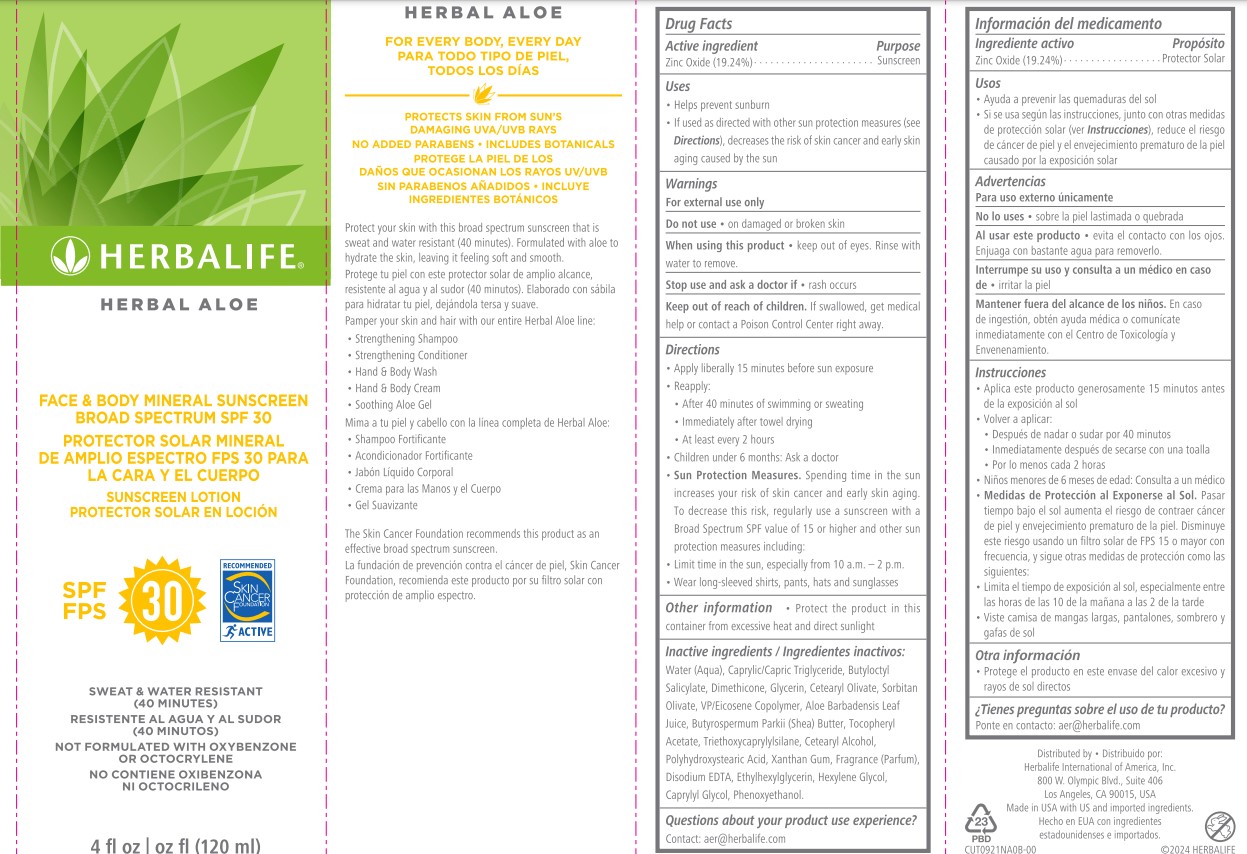 DRUG LABEL: Herbalife Herbal Aloe Face and Body Mineral Sunscreen Broad Spectrum SPF 30
NDC: 51785-922 | Form: CREAM
Manufacturer: Herbalife International of America, Inc.
Category: otc | Type: HUMAN OTC DRUG LABEL
Date: 20250121

ACTIVE INGREDIENTS: ZINC OXIDE 19.24 g/100 mL
INACTIVE INGREDIENTS: SORBITAN OLIVATE; ALPHA-TOCOPHEROL ACETATE; EDETATE DISODIUM; GLYCERIN; SHEA BUTTER; XANTHAN GUM; ETHYLHEXYLGLYCERIN; CAPRYLYL GLYCOL; WATER; MEDIUM-CHAIN TRIGLYCERIDES; POLYHYDROXYSTEARIC ACID (2300 MW); ALOE VERA LEAF; BUTYLOCTYL SALICYLATE; CETOSTEARYL ALCOHOL; DIMETHICONE 350; CETEARYL OLIVATE; PHENOXYETHANOL; VINYLPYRROLIDONE/EICOSENE COPOLYMER; TRIETHOXYCAPRYLYLSILANE; HEXYLENE GLYCOL

Herbalife Herbal Aloe Face and Body Mineral Sunscreen Broad Spectrum SPF 30

Drug Facts

Purpose

Sunscreen

Active ingredient

Zinc Oxide (19.24%)

Uses
• Helps prevent sunburn
• If used as directed with other sun protection measures (see
Directions), decreases the risk of skin cancer and early skin
aging caused by the sun

Warnings
For external use only

Do not use • on damaged or broken skin

When using this product • keep out of eyes. Rinse with
water to remove.

Stop use and ask a doctor if • rash occurs

Keep out of reach of children. If swallowed, get medical
help or contact a Poison Control Center right away.

Directions
• Apply liberally 15 minutes before sun exposure
• Reapply:
• After 40 minutes of swimming or sweating
• Immediately after towel drying
• At least every 2 hours
• Children under 6 months: Ask a doctor
• Sun Protection Measures. Spending time in the sun
increases your risk of skin cancer and early skin aging.
To decrease this risk, regularly use a sunscreen with a
Broad Spectrum SPF value of 15 or higher and other sun
protection measures including:
• Limit time in the sun, especially from 10 a.m. – 2 p.m.
• Wear long-sleeved shirts, pants, hats and sunglasses

Other information

• Protect the product in this
container from excessive heat and direct sunlight

Inactive ingredients:
Water (Aqua), Caprylic/Capric Triglyceride, Butyloctyl
Salicylate, Dimethicone, Glycerin, Cetearyl Olivate, Sorbitan
Olivate, VP/Eicosene Copolymer, Aloe Barbadensis Leaf Juice,
Butyrospermum Parkii (Shea) Butter, Tocopheryl Acetate,
Triethoxycaprylylsilane, Cetearyl Alcohol, Polyhydroxystearic
Acid, Xanthan Gum, Fragrance (Parfum), Disodium EDTA,
Ethylhexylglycerin, Hexylene Glycol, Caprylyl Glycol,
Phenoxyethanol.

Questions about your product use experience?

Contact: aer@herbalife.com

HERBAL ALOE

FOR EVERY BODY, EVERY DAY

PROTECTS SKIN FROM SUN’S
DAMAGING UVA/UVB RAYS
NO ADDED PARABENS • INCLUDES BOTANICALS
Protect your skin with this broad spectrum sunscreen that is
sweat and water resistant (40 minutes). Formulated with aloe to
hydrate the skin, leaving it feeling soft and smooth.
Pamper your skin and hair with our entire Herbal Aloe line:
• Strengthening Shampoo
• Strengthening Conditioner
• Hand & Body Wash
• Hand & Body Cream
• Soothing Aloe Gel
The Skin Cancer Foundation recommends this product as an
effective broad spectrum sunscreen.

Distributed by:
Herbalife International of America, Inc.
800 W. Olympic Blvd., Suite 406
Los Angeles, CA 90015, USA
Made in USA with US and imported ingredients.
CUT0921NA0B-00 ©2024 HERBALIFE

PACKAGE LABEL

HERBAL ALOE

FACE & BODY MINERAL SUNSCREEN
BROAD SPECTRUM SPF 30

SUNSCREEN LOTION

SPF 30

SWEAT & WATER RESISTANT
(40 MINUTES)

NOT FORMULATED WITH OXYBENZONE
OR OCTOCRYLENE

4 fl oz (120 ml)